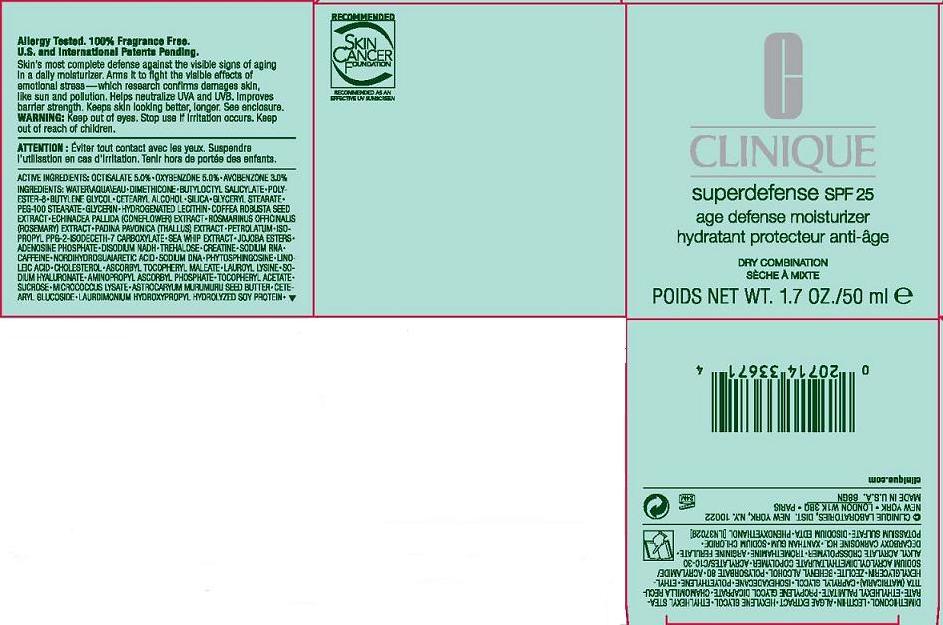 DRUG LABEL: SUPER DEFENSE
NDC: 49527-707 | Form: CREAM
Manufacturer: CLINIQUE LABORATORIES INC
Category: otc | Type: HUMAN OTC DRUG LABEL
Date: 20110628

ACTIVE INGREDIENTS: OXYBENZONE 5.0 mL/100 mL; OCTISALATE 5.0 mL/100 mL; AVOBENZONE 3.0 mL/100 mL
INACTIVE INGREDIENTS: WATER; DIMETHICONE; PETROLATUM; BUTYLENE GLYCOL; BUTYLOCTYL SALICYLATE; POLYGLYCERYL-4 ISOSTEARATE; MEDIUM-CHAIN TRIGLYCERIDES; GLYCERYL MONOSTEARATE; PEG-100 STEARATE; ROBUSTA COFFEE BEAN; ECHINACEA PALLIDA; ROSEMARY; PSEUDOPTEROGORGIA ELISABETHAE; SACCHAROMYCES LYSATE; TREHALOSE; CREATINE; CAFFEINE; MASOPROCOL; ASTROCARYUM MURUMURU SEED BUTTER; LINOLEIC ACID; CHOLESTEROL; LAMINARIA DIGITATA; HYALURONATE SODIUM; ALPHA-TOCOPHEROL ACETATE; ADENOSINE PHOSPHATE DISODIUM; MATRICARIA RECUTITA; ETHYLHEXYL STEARATE; CAPRYLYL GLYCOL; ISOHEXADECANE; LECITHIN, SOYBEAN; DOCOSANOL; XANTHAN GUM; POTASSIUM SULFATE; POLYSORBATE 80; STEARETH-21; SUCROSE; TROMETHAMINE; CARBOMER HOMOPOLYMER TYPE C; GLYCERIN; ETHYLHEXYL PALMITATE; PROPYLENE GLYCOL DICAPRATE; HEXYLENE GLYCOL; EDETATE DISODIUM; PHENOXYETHANOL; CETEARYL GLUCOSIDE; LAUROYL LYSINE; HYDROGENATED SOYBEAN LECITHIN

ACTIVE INGREDIENT

active ingredients: octisalate 5.00% [] oxybenzone 5.00% [] avobenzone 3.00%

INACTIVE INGREDIENT

inactive ingredients: water\aqua\eau [] dimethicone [] butyloctyl salicylate [] polyester-8 [] butylene glycol [] cetearyl alcohol [] silica [] glyceryl stearate [] peg-100 stearate [] glycerin [] hydrogenated lecithin [] coffea robusta seed extract [] echinacea pallida (coneflower) extract [] rosmarinus officinalis (rosemary) extract [] padina pavonica (thallus) extract [] petrolatum [] isopropyl ppg-2-isodeceth-7 carboxylate [] sea whip extract [] jojoba esters [] adenosine phosphate [] disodium nadh [] trehalose [] creatine [] sodium rna [] caffeine [] nordihydroguaiaretic acid [] sodium dna [] phytosphingosine [] linoleic acid [] cholesterol [] ascorbyl tocopheryl maleate [] lauroyl lysine [] sodium hyaluronate [] aminopropyl ascorbyl phosphate [] tocopheryl acetate [] sucrose [] micrococcus lysate [] astrocaryum murumuru seed butter [] cetearyl glucoside [] laurdimonium hydroxypropyl hydrolyzed soy protein [] dimethiconol [] lecithin [] algae extract [] hexylene glycol [] ethylhexyl stearate [] ethylhexyl palmitate [] propylene glycol dicaprate [] chamomilla recutita (matricaria) [] caprylyl glycol [] isohexadecane [] polyethylene [] ethylhexylglycerin [] zeolite [] behenyl alcohol [] polysorbate 80 [] acrylamide/sodium acryloyldimethyltaurate copolymer [] acrylates/c10-30 alkyl acrylate crosspolymer [] tromethamine [] arginine ferulate [] decarboxy carnosine hcl [] xanthan gum [] sodium chloride [] potassium sulfate [] disodium edta [] phenoxyethanol

WARNINGS

warning: keep out of eyes. stop use if irritation occurs. keep out of reach of children.

PACKAGE LABEL

PRINCIPAL DISPLAY PANEL:

CLINIQUE

SUPERDEFENSE SPF

AGE DEFENSE MOISTURIZER

SPF 25

DRY COMBINATION SKIN

NT WT. 1.7 OZ./50 ML

CLINIQUE LABORATORIES INC, DISTR

NEW YORK, NY 10022